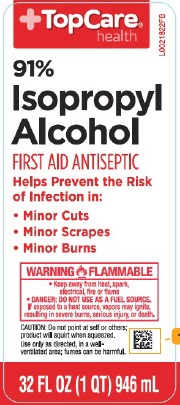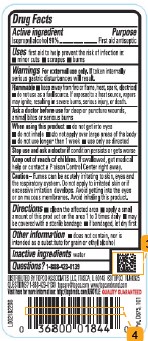 DRUG LABEL: Isopropyl Alcohol
NDC: 36800-804 | Form: LIQUID
Manufacturer: Topco Associates LLC
Category: otc | Type: HUMAN OTC DRUG LABEL
Date: 20260211

ACTIVE INGREDIENTS: ISOPROPYL ALCOHOL 91 mL/100 mL
INACTIVE INGREDIENTS: WATER

Top Care 804.003/804AA
91% Isopropyl Alcohol

Active Ingredient

Isopropyl alcohol 91%

Purpose

First aid antiseptic

Use

first aid to help prevent the risk of infection in:

- minor cuts
- scrapes
- burns

Warnings

For external use only. If taken internally serious gastric disturbances will result.

Flammable

- keep away from fire or flame, heat, spark, electrical
- do not use as a fuel source. If exposed to a heat source, vapors may ignite, resulting in severe burns, serious injury, or death.

Ask a doctor before use

for deep or puncture wounds, animal bites or serious burns

When using this product

- do not get into eyes
- do not inhale
- do not apply over large areas of the body
- do not use longer than 1 week
- use only as directed

Stop use and ask a doctor if

condition persists or gets worse

Keep out of reach of children.

If swallowed, get medical help or contact a Poison Control Center right away.

Caution

Fumes can be acutely irritating to skin, eyes and the respiratory system. Do not apply to irritated skin or if excessive irritation develops. Avoid getting into the eyes or on mucous membranes. Avoid inhaling this product.

Directions

- clean the affected area
- apply a small amount of this product on the area 1 to 3 times daily
- may be covered with a sterile bandage
- if bandaged, let dry first

Other information

- does not contain, nor is intended as a substitute for grain or ethyl alcohol

Inactive ingredient

water

Questions?

1-888-423-0139

Adverse Reaction

DISTRIBUTED BY TOPCO ASSOCIATES LLC, ITASCA, IL 60143 ©TOPCO

QUESTIONS? 1-888-423-0139 topcare@topcare.com www.topcarebrands.com

Visit here for more information: http://topbrnds.com QUALITY GUARANTEED

Pat. D675, 101

principal display panel

TopCare®

health

91% Isopropyl Alcohol

FIRST AID ANTISEPTIC

Helps Prevent the Risk of Infection in:

- Minor Cuts
- Minor Scrapes
- Minor Burns

WARNING FLAMMABLE

- Keep away from heat, spark, electrical, fire or flame
- DANGER: DO NOT USE AS A FUEL SOURCE.

If exposed to a heat source, vapors may ignite, resulting in severe burns, serious injury, or death.

CAUTION: Do not point at self or others; product will squirt whe squeezed.

Use only as directed, in a well-ventilated area; fumes can be harmful.

32 FL OZ (1 QT) 946 mL